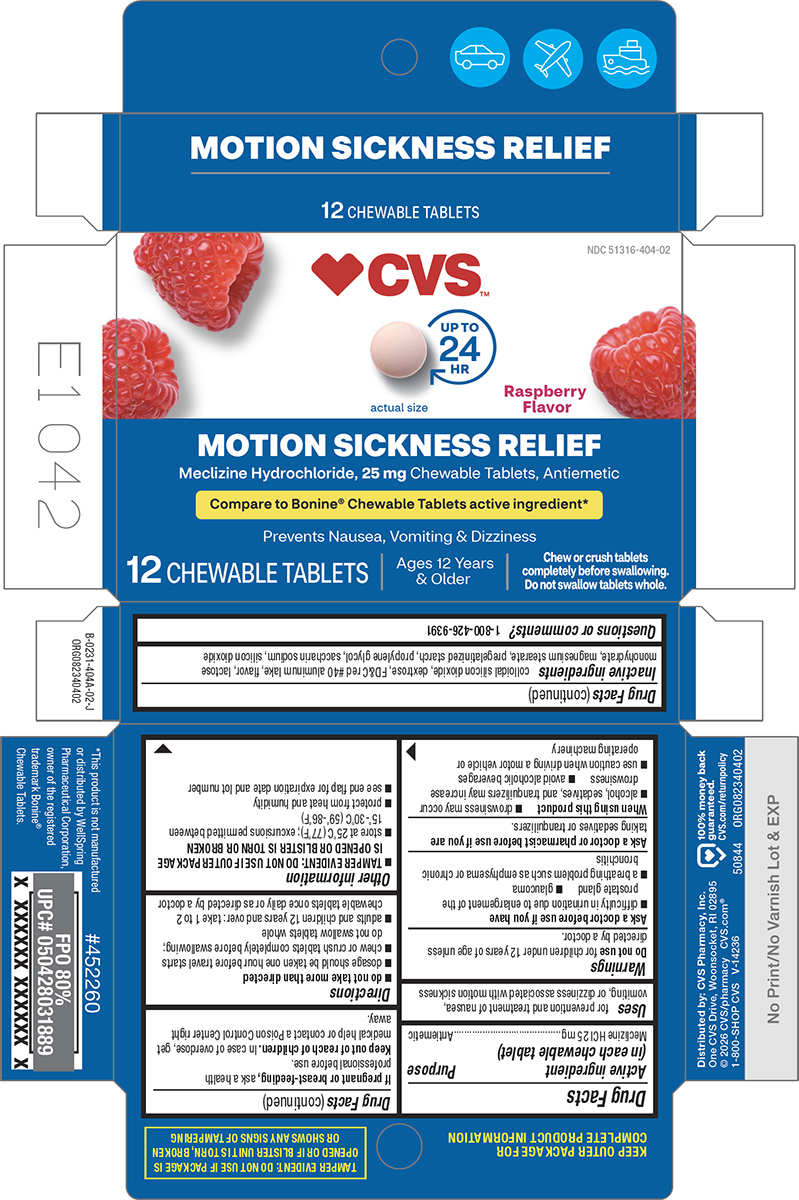 DRUG LABEL: Motion Sickness Relief
NDC: 51316-404 | Form: TABLET, CHEWABLE
Manufacturer: CVS WOONSOCKET PRESCRIPTION CENTER, INCORPORATED
Category: otc | Type: HUMAN OTC DRUG LABEL
Date: 20260120

ACTIVE INGREDIENTS: MECLIZINE HYDROCHLORIDE 25 mg/1 1
INACTIVE INGREDIENTS: SILICON DIOXIDE; DEXTROSE, UNSPECIFIED FORM; FD&C RED NO. 40 ALUMINUM LAKE; LACTOSE MONOHYDRATE; MAGNESIUM STEARATE; STARCH, CORN; PROPYLENE GLYCOL; SACCHARIN SODIUM

CVS 44-404A-Motion Sickness Relief

Active ingredient (in each chewable tablet)

Meclizine HCl 25 mg

Purpose

Antiemetic

Uses

for prevention and treatment of nausea, vomiting, or dizziness associated with motion sickness

Warnings

Do not use

for children under 12 years of age unless directed by a doctor.

Ask a doctor before use if you have

- difficulty in urination due to enlargement of the prostate gland
- glaucoma
- a breathing problem such as emphysema or chronic bronchitis

Ask a doctor or pharmacist before use if you are

taking sedatives or tranquilizers.

When using this product

- drowsiness may occur
- alcohol, sedatives, and tranquilizers may increase drowsiness
- avoid alcoholic beverages
- use caution when driving a motor vehicle or operating machinery

If pregnant or breast-feeding,

ask a health professional before use.

Keep out of reach of children.

In case of overdose, get medical help or contact a Poison Control Center right away.

Directions

- do not take more than directed
- dosage should be taken one hour before travel starts
- chew or crush tablets completely before swallowing; do not swallow tablets whole
- adults and children 12 years and over: take 1 to 2 chewable tablets once daily or as directed by a doctor

Other information

- TAMPER EVIDENT: DO NOT USE IF OUTER PACKAGE IS OPENED OR BLISTER IS TORN OR BROKEN
- store at 25°C (77°F); excursions permitted between 15°-30°C (59°-86°F)
- protect from heat and humidity
- see end flap for expiration date and lot number

Inactive ingredients

colloidal silicon dioxide, dextrose, FD&C red #40 aluminum lake, flavor, lactose monohydrate, magnesium stearate, pregelatinized starch, propylene glycol, saccharin sodium, silicon dioxide

Questions or comments?

1-800-426-9391

Principal Display Panel

♥CVS™

NDC 51316-404-02

UP TO
24
HR

actual size

Raspberry
Flavor

MOTION SICKNESS RELIEF
Meclizine Hydrochloride, 25 mg Chewable Tablets, Antiemetic

Compare to Bonine® Chewable Tablets active ingredient*

Prevents Nausea, Vomiting & Dizziness

12 CHEWABLE TABLETS

Ages 12 Years
& Older

Chew or crush tablets
completely before swallowing.
Do not swallow tablets whole.

TAMPER EVIDENT: DO NOT USE IF PACKAGE IS
OPENED OR IF BLISTER UNIT IS TORN, BROKEN
OR SHOWS ANY SIGNS OF TAMPERING

*This product is not manufactured
or distributed by WellSpring
Pharmaceutical Corporation,
owner of the registered
trademark Bonine®
Chewable Tablets.

Distributed by: CVS Pharmacy, Inc.
One CVS Drive, Woonsocket, RI 02895
© 2026 CVS/pharmacy CVS.com®
1-800-SHOP CVS V-14236

100% money back
guaranteed.
CVS.com/returnpolicy

50844 ORG082340402

CVS 44-404A